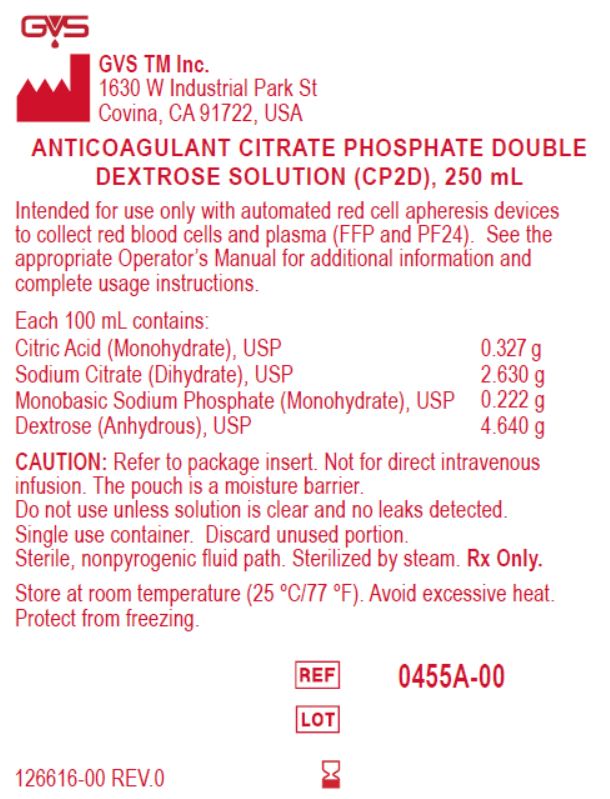 DRUG LABEL: CP2D
NDC: 87069-455 | Form: SOLUTION
Manufacturer: GVS TM INC
Category: prescription | Type: HUMAN PRESCRIPTION DRUG LABEL
Date: 20251106

ACTIVE INGREDIENTS: DEXTROSE, UNSPECIFIED FORM 4.64 g/100 mL
INACTIVE INGREDIENTS: CITRIC ACID MONOHYDRATE; SODIUM CITRATE; MONOBASIC POTASSIUM PHOSPHATE

CP2D listing

INTENDED USE OF THE DEVICE

Intended for use only with automated red cell apheresis devices
to collect red blood cells and plasma (FFP and PF24).

Storage and handling section

Store at room temperature (25 °C/77 °F). Avoid excessive heat.
Protect from freezing.

Warnings and precautions

Warnings

Not for direct intravenous infusion.

Single-use container – discard unused portion. (do not reuse)

Do not use unless the solution is clear and no leaks are detected.

Precautions

Use only with automated red-cell apheresis devices and follow the Operator’s Manual.

Refer to the package insert for complete instructions.

Storage/handling: Store at 25 °C/77 °F, avoid excessive heat, protect from freezing.

Pouch is a moisture barrier; handle to maintain package integrity.

Description section

ANTICOAGULANT CITRATE PHOSPHATE DOUBLE

DEXTROSE SOLUTION (CP2D), 250 mL

0455A-00

Statement of identity

ANTICOAGULANT CITRATE PHOSPHATE DOUBLE
DEXTROSE SOLUTION (CP2D), 250 mL

0455A-00

Package label

Manufacturer information: GVS TM Inc.
1630 W Industrial Park St
Covina, CA 91722, USA

ANTICOAGULANT CITRATE PHOSPHATE DOUBLE
DEXTROSE SOLUTION (CP2D), 250 mL

Intended for use only with automated red cell apheresis devices
to collect red blood cells and plasma (FFP and PF24). See the
appropriate Operator’s Manual for additional information and
complete usage instructions.
Each 100 mL contains:
Citric Acid (Monohydrate), USP 0.327 g
Sodium Citrate (Dihydrate), USP 2.630 g
Monobasic Sodium Phosphate (Monohydrate), USP 0.222 g
Dextrose (Anhydrous), USP 4.640 g
CAUTION: Refer to package insert. Not for direct intravenous
infusion. The pouch is a moisture barrier.
Do not use unless solution is clear and no leaks detected.
Single use container. Discard unused portion.
Sterile, nonpyrogenic fluid path. Sterilized by steam. Rx Only.
Store at room temperature (25 °C/77 °F). Avoid excessive heat.
Protect from freezing.

REF: 0455A-00

lot and expiry date

126616-00 REV.0 - template number